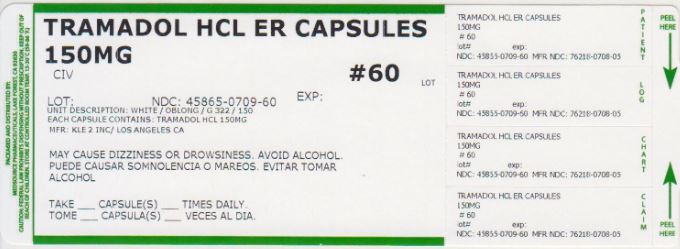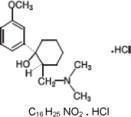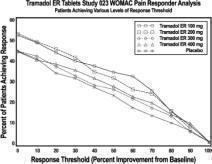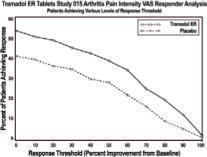 DRUG LABEL: Tramadol Hydrochloride
NDC: 45865-709 | Form: CAPSULE, EXTENDED RELEASE
Manufacturer: Medsource Pharmaceuticals
Category: prescription | Type: HUMAN PRESCRIPTION DRUG LABEL
Date: 20191227
DEA Schedule: CIV

ACTIVE INGREDIENTS: TRAMADOL HYDROCHLORIDE 150 mg/1 1
INACTIVE INGREDIENTS: GELATIN; TITANIUM DIOXIDE; SHELLAC; FERRIC OXIDE YELLOW; LACTOSE MONOHYDRATE; CELLULOSE, MICROCRYSTALLINE; SUCROSE STEARATE; POVIDONE K30; STARCH, CORN; MAGNESIUM STEARATE; HYPROMELLOSE 2910 (6 MPA.S); TALC; POLYSORBATE 80; ETHYL ACRYLATE AND METHYL METHACRYLATE COPOLYMER (2:1; 750000 MW)

HIGHLIGHTS OF PRESCRIBING INFORMATION

These highlights do not include all the information needed to use Tramadol Hydrochloride Extended-Release safely and effectively. See full prescribing information for Tramadol Hydrochloride Extended-Release.
Tramadol Hydrochloride Extended-Release (tramadol hydrochloride) Extended-Release Capsules
Initial U.S. Approval: 1995

1 INDICATIONS AND USAGE

Tramadol Hydrochloride Extended-Release is an opioid agonist indicated for the management of moderate to moderately severe chronic pain in adults who require around-the-clock treatment of their pain for an extended period of time. (1)

2 DOSAGE AND ADMINISTRATION

- Tramadol Hydrochloride Extended-Release must be swallowed whole, and must not be split, chewed, dissolved or crushed. (2.1)
- Do not exceed a daily dose of 300 mg tramadol. Do not use with other tramadol products. (2.1)
- Adults not on tramadol Immediate-Release (IR): Initiate Tramadol Hydrochloride Extended-Release at a dose of 100 mg once daily, then titrate up by 150 mg, 200 mg and 300 mg, every 5 days according to need and tolerance. (2.1)
- Adults on tramadol IR: Calculate total 24-hr IR dose, initiate Tramadol Hydrochloride Extended-Release at a dose rounded down to next lower dose; then adjust dose according to need and tolerance. (2.1)
- Patients >65 years of age: Initiate dosing cautiously; use even greater caution in patients >75 years. (2.3)
- May be taken without regard to meals. (12.3)

3 DOSAGE FORMS AND STRENGTHS

Extended-Release Capsules: 150 mg (3)

4 CONTRAINDICATIONS

- Patients who have previously demonstrated hypersensitivity to tramadol, any other component of this product or opioids. (4)
- Patients with significant respiratory depression in unmonitored settings or the absence of resuscitative equipment. (4)
- Patients with acute or severe bronchial asthma or hypercapnia in unmonitored settings or the absence of resuscitative equipment. (4)
- All other opioid contraindications, including intoxication with alcohol, hypnotics, narcotics, centrally acting analgesics, opioids or psychotropic drugs. (4)

5 WARNINGS AND PRECAUTIONS

- Seizures: Can occur within the recommended dose range. Concomitant use with certain other drugs may increase the seizure risk. Risk of convulsions may increase in patients with epilepsy, history of seizures, and with a recognized risk for seizure. (5.1, 5.9)
- Suicide: Do not prescribe for suicidal or addiction-prone patients. (5.2)
- Serotonin Syndrome: May be life-threatening. Can occur with tramadol alone or with concomitant use of other serotonergic drugs or those that inhibit metabolism of tramadol. (5.3. 5.9)
- Anaphylactoid Reactions: Serious and rarely fatal anaphylactoid reactions have occurred. Increased risk in patients with history of anaphylactoid reactions to other opioids. (5.4)
- Hypersensitivity reactions: Serious and rarely fatal anaphylactoid reactions have occurred, often after the first dose. Other reactions include pruritus, hives, bronchospasm, angioedema, TEN, SJS. (5.4)
- Respiratory Depression: Administer cautiously in patients at risk for respiratory depression. (5.5)
- CNS Depression: Use with caution and in reduced dosages in patients taking CNS depressants and in patients at risk for CNS depression. Patients should not consume alcohol-containing beverages while using Tramadol Hydrochloride Extended-Release (5.6, 5.12)
- Increased Intracranial Pressure or Head Trauma: Use with caution in patients with increased intracranial pressure or head injury. (5.7)
- Ambulatory Patients: Tramadol may impair mental and/or physical abilities required for potentially hazardous tasks. (5.8)
- Tapering may reduce withdrawal symptoms. (5.10)
- Misuse, Abuse, and Diversion: Tramadol can be abused in a manner similar to other opioid agonists, legal or illicit. (5.11)
- Overdosage can cause CNS and respiratory depression and death. (5.13)
- Tramadol Hydrochloride Extended-Release may complicate clinical assessment of acute abdominal conditions. (5.14)

6 ADVERSE REACTIONS

Most common adverse reactions (incidence ≥ 10% and twice placebo) are nausea, constipation, dry mouth, somnolence, dizziness, and vomiting. (6)

To report SUSPECTED ADVERSE REACTIONS, contact Vertical at (877) 958-3784 or FDA at 1-800-FDA-1088 or www.fda.gov/medwatch.

7 DRUG INTERACTIONS

- SSRI/SNRI antidepressants or anorectics, TCA antidepressants, other tricyclic compounds, other opioids, MAOIs, neuroleptics or other drugs that lower seizure threshold: Risk of seizures increased with concomitant use of tramadol. (7.1)
- CYP2D6 and/or CYP3A4 Inhibitors: May result in increased tramadol concentrations. (7.2)
- Serotonergic Drugs, Triptans, and CNS Depressants: Enhanced risk of adverse reactions. (7.3, 7.4, and 7.5)
- Carbamazepine: Reduces analgesic effects of tramadol. (7.6)
- Quinidine: May result in increased concentration of tramadol and reduced concentrations of its active metabolite, M1. (7.7)
- Digoxin and Warfarin: Rare reports of digoxin toxicity; altered warfarin effect and elevation of prothrombin time. (7.8)

8 USE IN SPECIFIC POPULATIONS

- Pregnancy: Use only if benefit outweighs risk to the fetus. Neonatal seizures and withdrawal syndrome, fetal death and still birth have occurred. (8.1)
- Labor and Delivery: Tramadol crosses the placenta, and should not be used prior to or during labor unless the potential benefits outweigh the risks. Long term use during pregnancy can cause dependence and withdrawal symptoms in the newborn. (8.2)
- Nursing mothers: Effect on child not studied. Tramadol Hydrochloride Extended-Release should not be used. (8.3)
- Pediatrics: Safety and effectiveness of tramadol has not been established in patients under 18 years. Use in this population is not recommended. (8.4)
- Elderly: Use with caution, in particular in patients older than 75 years. (8.5)
- Severe renal impairment: Tramadol Hydrochloride Extended-Release should not be used. (8.6)
- Severe hepatic impairment: Tramadol Hydrochloride Extended-Release should not be used. (8.7)

FULL PRESCRIBING INFORMATION

1 INDICATIONS AND USAGE

Tramadol Hydrochloride Extended-Release is indicated for the management of moderate to moderately severe chronic pain in adults who require around-the-clock treatment of their pain for an extended period of time.

2 DOSAGE AND ADMINISTRATION

2.1 General Dosing Considerations

Tramadol Hydrochloride Extended-Release is an extended-release formulation intended for once a day dosing in adults aged 18 years and older. The tablets must be swallowed whole with liquid and must not be split, chewed, dissolved or crushed. Chewing, crushing or splitting the tablet could result in the uncontrolled delivery of tramadol, in overdose and death [see WARNINGS AND PRECAUTIONS (5.11), DRUG ABUSE AND DEPENDENCE (9), and OVERDOSE (10.1)].

Do not administer Tramadol Hydrochloride Extended-Release at a dose exceeding 300 mg per day. Do not use Tramadol Hydrochloride Extended-Release more than once daily or concomitantly with other tramadol products [see WARNINGS AND PRECAUTIONS (5.12)].

2.2 Patients Not Currently on Tramadol Immediate-Release Products

Initiate treatment with Tramadol Hydrochloride Extended-Release at a dose of 100 mg once daily and titrated up as necessary to 150 mg, 200 mg and 300 mg every five days to achieve a balance between relief of pain and tolerability.

2.3 Patients Currently on Tramadol Immediate-Release Products

Calculate the 24-hour tramadol IR dose and initiate a total daily dose of Tramadol Hydrochloride Extended-Release rounded down to the next lowest 100 mg increment. The dose may subsequently be individualized according to patient need. Due to limitations in flexibility of dose selection with Tramadol Hydrochloride Extended-Release, some patients maintained on tramadol IR products may not be able to convert to Tramadol Hydrochloride Extended-Release.

2.4 Patients 65 Years of Age and Older

Initiate dosing of an elderly patient (over 65 years of age) should be initiated cautiously, usually starting at the low end of the dosing range, reflecting the greater frequency of decreased hepatic, renal or cardiac function and of concomitant disease or other drug therapy. Tramadol Hydrochloride Extended-Release should be administered with even greater caution in patients over 75 years, due to the greater frequency of adverse events seen in this population.

2.5 Patients with Renal Impairment

The limited availability of dose strengths and once daily dosing of Tramadol Hydrochloride Extended-Release do not permit the dosing flexibility required for safe use in patients with severe renal impairment. Do not use Tramadol Hydrochloride Extended-Release in patients with creatinine clearance less than 30 mL/min [see USE IN SPECIFIC POPULATIONS (8.6) and CLINICAL PHARMACOLOGY (12.3) ].

2.6 Patients with Hepatic Impairment

The limited availability of dose strengths and once daily dosing of tramadol hydrochloride extended-release capsules do not permit the dosing flexibility required for safe use in patients with severe hepatic impairment. Do not use Tramadol Hydrochloride Extended-Release in patients with severe hepatic impairment (Child-Pugh Class C) [see USE IN SPECIFIC POPULATIONS (8.7) and CLINICAL PHARMACOLOGY (12.3) ].

2.7 Discontinuation of Treatment

Withdrawal symptoms may occur if Tramadol Hydrochloride Extended-Release is discontinued abruptly. Clinical experience with tramadol suggests that withdrawal symptoms may be reduced by tapering Tramadol Hydrochloride Extended-Release [see WARNINGS AND PRECAUTIONS (5.10) and DRUG ABUSE AND DEPENDENCE (9.3)] .

2.8 Food Effects

Tramadol Hydrochloride Extended-Release may be taken without regard to food [see CLINICAL PHARMACOLOGY (12.3)].

3 DOSAGE FORMS AND STRENGTHS

Tramadol Hydrochloride Extended-Release is available in 150 mg capsules.

150 mg Capsules: White capsule imprinted with gold ink “ G 322” on cap and “ 150” between lines on the body

4 CONTRAINDICATIONS

Tramadol Hydrochloride Extended-Release is contraindicated in patients who have previously demonstrated hypersensitivity to tramadol, any other component of Tramadol Hydrochloride Extended-Release, or opioids. Reactions range from pruritis to fatal anaphylactoid reactions [see WARNINGS AND PRECAUTIONS (5.4)].

Tramadol Hydrochloride Extended-Release is contraindicated in patients with significant respiratory depression in unmonitored settings or the absence of resuscitative equipment.

Tramadol Hydrochloride Extended-Release is contraindicated in patients with acute or severe bronchial asthma or hypercapnia in unmonitored settings or the absence of resuscitative equipment.

5 WARNINGS AND PRECAUTIONS

5.1 Seizure Risk

Seizures have been reported in patients receiving tramadol within the recommended dosage range. Spontaneous post-marketing reports indicate that seizure risk is increased with doses of tramadol above the recommended range. Concomitant use of tramadol increases the seizure risk in patients taking: [see DRUG INTERACTIONS (7.1, 7.2)]

- Selective serotonin reuptake inhibitors and serotonin-norepinephrine reuptake inhibitors (SNRIs) antidepressants or anorectics,
- Tricyclic antidepressants (TCAs), and other tricyclic compounds (e.g., cyclobenzaprine, promethazine, etc.),
- Other opioids,
- MAO inhibitors [see WARNINGS AND PRECAUTIONS (5.9) and DRUG INTERACTIONS (7.1)],
- Neuroleptics, or
- Other drugs that reduce the seizure threshold.

Risk of seizures may also increase in patients with epilepsy, those with a history of seizures, or in patients with a recognized risk for seizure (such as head trauma, metabolic disorders, alcohol and drug withdrawal, CNS infections).

In tramadol overdose, naloxone administration may increase the risk of seizure.

5.2 Suicide Risk

- Do not prescribe Tramadol Hydrochloride Extended-Release for patients who are suicidal or addiction-prone. Consideration should be given to the use of non-narcotic analgesics in patients who are suicidal or depressed [see DRUG ABUSE AND DEPENDENCE (9.2) ].
- Prescribe Tramadol Hydrochloride Extended-Release with caution for patients with a history of misuse and/or are taking CNS-active drugs including tranquilizers or antidepressant drugs, or alcohol in excess, and patients who suffer from emotional disturbance or depression [see DRUG INTERACTIONS (7.4)].
- Tell your patients not to exceed the recommended dose and to limit their intake of alcohol [see DOSAGE AND ADMINISTRATION (2.1) and WARNINGS AND PRECAUTIONS (5.6)] .

5.3 Serotonin Syndrome Risk

The development of a potentially life-threatening serotonin syndrome may occur with use of tramadol products, including Tramadol Hydrochloride Extended-Release , particularly with concomitant use of serotonergic drugs such as SSRIs, SNRIs, TCAs, MAOIs and triptans, with drugs which impair metabolism of serotonin (including MAOIs) and with drugs which impair metabolism of tramadol (CYP2D6 and CYP3A4 inhibitors). This may occur within the recommended dose. [see CLINICAL PHARMACOLOGY (12.3)] .

Serotonin syndrome may include mental-status changes (e.g., agitation, hallucinations, coma), autonomic instability (e.g., tachycardia, labile blood pressure, hyperthermia), neuromuscular aberrations (e.g., hyperreflexia, incoordination) and/or gastrointestinal symptoms (e.g., nausea, vomiting, diarrhea).

5.4 Anaphylactoid Reactions

Serious and rarely fatal anaphylactoid reactions have been reported in patients receiving therapy with tramadol. When these events do occur it is often following the first dose. Other reported allergic reactions include pruritus, hives, bronchospasm, angioedema, toxic epidermal necrolysis and Stevens-Johnson syndrome. Patients with a history of anaphylactoid reactions to codeine and other opioids may be at increased risk and therefore should not receive Tramadol Hydrochloride Extended-Release [see CONTRAINDICATIONS (4)].

5.5 Respiratory Depression

Administer Tramadol Hydrochloride Extended-Release cautiously in patients at risk for respiratory depression. In these patients alternative non-opioid analgesics should be considered. If large doses of tramadol are administered with anesthetic medications or alcohol, respiratory depression may result. Respiratory depression should be treated as an overdose. If naloxone is to be administered, use cautiously because it may precipitate seizures [see WARNINGS AND PRECAUTIONS (5.1) and OVERDOSAGE (10)] .

5.6 Interaction With Central Nervous System (CNS) Depressants, Including Alcohol and Drugs of Abuse

Tramadol may be expected to have additive effects when used in conjunction with alcohol, other opioids, or illicit drugs that cause central nervous system depression. Use Tramadol Hydrochloride Extended-Release with caution and in reduced dosages when administered to patients receiving CNS depressants such as alcohol, opioids, anesthetic agents, narcotics, phenothiazines, tranquilizers or sedative hypnotics. Tramadol Hydrochloride Extended-Release increases the risk of CNS and respiratory depression in these patients. Alcohol-containing beverages should not be consumed by patients using Tramadol Hydrochloride Extended-Release [see WARNINGS AND PRECAUTIONS (5.6), DRUG INTERACTIONS (7.4), and OVERDOSAGE (10)] .

5.7 Patients with Increased Intracranial Pressure or Head Trauma

Use Tramadol Hydrochloride Extended-Release with caution in patients with increased intracranial pressure or head injury. The respiratory depressant effects of opioids include carbon dioxide retention and secondary elevation of cerebrospinal fluid pressure, and may be markedly exaggerated in these patients. Additionally, pupillary changes (miosis) from tramadol may obscure the existence, extent, or course of intracranial pathology. Clinicians should also maintain a high index of suspicion for adverse drug reaction when evaluating altered mental status in these patients if they are receiving Tramadol Hydrochloride Extended-Release [see WARNINGS AND PRECAUTIONS (5.5)] .

5.8 Use in Ambulatory Patients

Tramadol Hydrochloride Extended-Release may impair the mental and or physical abilities required for the performance of potentially hazardous tasks such as driving a car or operating machinery. Caution patients initiating therapy with Tramadol Hydrochloride Extended-Release or those whose dose has been increased to refrain from potentially hazardous activities until it is established that their mental and physical abilities are not significantly impaired.

5.9 Use With MAO Inhibitors and SSRIs

Use Tramadol Hydrochloride Extended-Release with great caution in patients taking monoamine oxidase inhibitors. Animal studies have shown increased deaths with combined administration. Concomitant use of Tramadol Hydrochloride Extended-Release with MAO inhibitors or SSRI's increases the risk of adverse reactions, including seizure and serotonin syndrome [see WARNINGS AND PRECAUTIONS (5.1, 5.3)] .

5.10 Withdrawal Symptoms

Withdrawal symptoms may occur if Tramadol Hydrochloride Extended-Release is discontinued abruptly. These symptoms may include: anxiety, sweating, insomnia, rigors, pain, nausea, tremors, diarrhea, upper respiratory symptoms, piloerection, and rarely hallucinations. Clinical experience with other formulations of tramadol suggests that withdrawal symptoms may be reduced by tapering Tramadol Hydrochloride Extended-Release when discontinuing tramadol therapy.

5.11 Misuse, Abuse and Diversion of Opioids

Tramadol Hydrochloride Extended-Release contains tramadol, an opioid agonist of the morphine-type. Such drugs are sought by drug abusers and people with addiction disorders and are subject to criminal diversion.

Tramadol can be abused in a manner similar to other opioid agonists, legal or illicit. This should be considered when prescribing or dispensing Tramadol Hydrochloride Extended-Release in situations where the physician or pharmacist is concerned about an increased risk of misuse, abuse, or diversion.

Tramadol Hydrochloride Extended-Release could be abused by crushing, chewing, snorting, or injecting the dissolved product. These practices will result in the uncontrolled delivery of the opioid and pose a significant risk to the abuser that could result in overdose and death [see WARNINGS AND PRECAUTIONS (5.13), DRUG ABUSE AND DEPENDENCE (9), and OVERDOSAGE (10)] .

Concerns about abuse, addiction, and diversion should not prevent the proper management of pain. The development of addiction to opioid analgesics in properly managed patients with pain has been reported to be rare. However, data are not available to establish the true incidence of addiction in chronic pain patients.

Healthcare professionals should contact their State Professional Licensing Board, or State Controlled Substances Authority for information on how to prevent and detect abuse or diversion of this product.

5.12 Risk of Overdosage

Serious potential consequences of overdosage with Tramadol Hydrochloride Extended-Release are central nervous system depression, respiratory depression and death. In treating an overdose, primary attention should be given to maintaining adequate ventilation along with general supportive treatment [see OVERDOSAGE (10)].

5.13 Acute Abdominal Conditions

The administration of Tramadol Hydrochloride Extended-Release may complicate the clinical assessment of patients with acute abdominal conditions.

6 ADVERSE REACTIONS

The following serious or otherwise important adverse reactions are described in greater detail, in other sections:

- - Seizure risk [ see WARNINGS AND PRECAUTIONS (5.1) ]
- - Suicide risk [ see WARNINGS AND PRECAUTIONS (5.2) ]
- - Serotonin syndrome [ see WARNINGS AND PRECAUTIONS (5.3) ]
- - Anaphylactoid and allergic reactions [ see WARNINGS AND PRECAUTIONS (5.4) ]
- - Respiratory depression [ see WARNINGS AND PRECAUTIONS (5.5) ]
- - Withdrawal symptoms [ see WARNINGS AND PRECAUTIONS (5.10) ]

6.1 Clinical Studies Experience

Because clinical trials are conducted under widely varying conditions, adverse reaction rates observed in the clinical trials of a drug cannot be directly compared to rates in the clinical trials of another drug and may not reflect the rates observed in practice.

Tramadol Hydrochloride Extended-Release capsules were administered to a total of 1987 patients in clinical trials. These included four double-blind and one long-term, open-label study in patients with osteoarthritis of the hip and knee. A total of 812 patients were 65 years or older. Adverse reactions with doses from 100 mg to 300 mg in the four pooled, randomized, double-blind, placebo-controlled studies in patients with chronic non-malignant pain are presented in the following table (see Table 1).

Table 1: Incidence (%) of patients with adverse reaction rates ≥ 5% from four double-blind, placebo controlled studies in patients with moderate to moderately severe chronic pain by dose (N=1917).
 | Tramadol Hydrochloride Extended-Release |  |  | PLACEBO
Preferred Term | 100 mg (N=429) n (%) | 200 mg (N=434) n (%) | 300 mg (N=1054) n (%) | (N=646) n (%)
Headache | 99 (23.1) | 96 (22.1) | 200 (19.0) | 128 (19.8)
Nausea | 69 (16.1) | 93 (21.4) | 265 (25.1) | 37 (5.7)
Somnolence | 50 (11.7) | 60 (13.8) | 170 (16.1) | 26 (4.0)
Dizziness | 41 (9.6) | 54 (12.4) | 143 (13.6) | 31 (4.8)
Constipation | 40 (9.3) | 59 (13.6) | 225 (21.3) | 27 (4.2)
Vomiting | 28 (6.5) | 45 (10.4) | 98 (9.3) | 12 (1.9)
Arthralgia | 23 (5.4) | 20 (4.6) | 53 (5.0) | 33 (5.1)
Dry Mouth | 20 (4.7) | 36 (8.3) | 138 (13.1) | 22 (3.4)
Sweating | 18 (4.2) | 23 (5.3) | 71 (6.7) | 4 (0.6)
Asthenia | 15 (3.5) | 26 (6.0) | 91 (8.6) | 17 (2.6)
Pruritus | 13 (3.0) | 25 (5.8) | 77 (7.3) | 12 (1.9)
Anorexia | 9 (2.1) | 23 (5.3) | 60 (5.7) | 1 (0.2)
Insomnia | 9 (2.1) | 9 (2.1) | 53 (5.0) | 11 (1.7)

The following adverse reactions were reported from all chronic pain studies (N=1917). The lists below include adverse reactions not otherwise noted in Table 1.

Adverse reactions with incidence rates of 1.0% to <5.0%

Cardiac disorders: hypertension
Gastrointestinal disorders: dyspepsia, flatulence
General disorders: abdominal pain, accidental injury, chills, fever, flu syndrome, neck pain, pelvic pain
Investigations: hyperglycemia, urine abnormality
Metabolism and nutrition disorders: peripheral edema, weight loss
Musculoskeletal, connective tissue and bone disorders: myalgia
Nervous system disorders: paresthesia, tremor, withdrawal syndrome
Psychiatric disorders: agitation, anxiety, apathy, confusion, depersonalization, depression, euphoria, nervousness
Respiratory, thoracic and mediastinal disorders: bronchitis, pharyngitis, rhinitis, sinusitis
Skin and subcutaneous tissue disorders: rash
Urogenital disorders: prostatic disorder, urinary tract infection
Vascular disorders: vasodilatation

Adverse reactions with incidence rates of 0.5% to <1.0% at any dose and serious adverse reactions reported in at least two patients.

Cardiac disorders: EKG abnormal, hypotension, tachycardia
Gastrointestinal disorders: gastroenteritis
General disorders: neck rigidity, viral infection
Hematologic/Lymphatic disorders; anemia, ecchymoses
Metabolism and nutrition disorders: blood urea nitrogen increased, GGT increased, gout, SGPT increased
Musculoskeletal disorders: arthritis, arthrosis, joint disorder, leg cramps
Nervous system disorders: emotional lability, hyperkinesia, hypertonia, thinking abnormal, twitching, vertigo
Respiratory disorders: pneumonia
Skin and subcutaneous tissue disorders: hair disorder, skin disorder, urticaria
Special Senses: eye disorder, lacrimation disorder
Urogenital disorders: cystitis, dysuria, sexual function abnormality, urinary retention

7 DRUG INTERACTIONS

7.1 Drugs Affecting Seizure Threshold

Concomitant use of tramadol increases the seizure risk in patients taking SSRI/SNRI antidepressants or anorectics, TCA antidepressants and other tricyclic compounds, other opioids, MAOIs, neuroleptics or other drugs that lower the seizure threshold [see WARNINGS AND PRECAUTIONS (5.1) ].

7.2 CYP2D6 and/or CYP3A4 inhibitors

Tramadol is metabolized by CYP2D6 to form the active metabolite, O-desmethyl tramadol (M1). In vitro drug interaction studies in human liver microsomes indicate that concomitant administration with inhibitors of CYP2D6 such as fluoxetine, paroxetine, and amitriptyline could result in some inhibition of the metabolism of tramadol.

Tramadol is also metabolized by CYP3A4 [see CLINICAL PHARMACOLOGY (12.3)] . Administration of CYP3A4 inhibitors, such as ketoconazole and erythromycin with Tramadol Hydrochloride Extended-Release may affect the metabolism of tramadol leading to altered tramadol exposure.

Concomitant administration of CYP2D6 and/or CYP3A4 inhibitors, such as quinidine, fluoxetine, paroxetine and amitriptyline (CYP2D6 inhibitors), and ketoconazole and erythromycin (CYP3A4 inhibitors), may reduce metabolic clearance of tramadol increasing the risk for serious adverse events including seizures and serotonin syndrome [see CLINICAL PHARMACOLOGY (12.3)] .

7.3 Serotonergic Drugs

There have been post-marketing reports of serotonin syndrome with use of tramadol and SSRIs/SNRIs or MAOIs and α2-adrenergic blockers. Caution is advised when Tramadol Hydrochloride Extended-Release is co-administered with other drugs that may affect the serotonergic neurotransmitter systems, such as SSRIs, MAOIs, triptans, linezolid (an antibiotic which is a reversible non-selective MAOI), lithium, or St. John's Wort. If concomitant treatment of Tramadol Hydrochloride Extended-Release with a drug affecting the serotonergic neurotransmitter system is clinically warranted, careful observation of the patient is advised, particularly during treatment initiation and dose increases [see WARNINGS AND PRECAUTIONS (5.3)].

7.4 Triptans

Based on the mechanism of action of tramadol and the potential for serotonin syndrome, caution is advised when Tramadol Hydrochloride Extended-Release is co-administered with a triptan. If concomitant treatment of Tramadol Hydrochloride Extended-Release with a triptan is clinically warranted, careful observation of the patient is advised, particularly during treatment initiation and dose increases [see WARNINGS AND PRECAUTIONS (5.3)].

7.5 Interaction With Central Nervous System (CNS) Depressants

Tramadol Hydrochloride Extended-Release should be used with caution and in reduced dosages when administered to patients receiving CNS depressants such as opioids, anesthetic agents, narcotics, phenothiazines, tranquilizers or sedative hypnotics. Tramadol Hydrochloride Extended-Release increases the risk of CNS and respiratory depression in these patients [see WARNINGS AND PRECAUTIONS (5.6)].

7.6 Quinidine

Quinidine is a strong inhibitor of CYP2D6. Coadministration of quinidine with an extended-release tramadol product resulted in a 50-60% increase in tramadol exposure and a 50-60% decrease in M1 exposure. The clinical consequences of these findings are unknown. [see CLINICAL PHARMACOLOGY (12.3)]. In vitro drug interaction studies in human liver microsomes indicate that tramadol has no effect on quinidine metabolism.

7.7 Digoxin and Warfarins

Post-marketing surveillance of tramadol has revealed rare reports of digoxin toxicity and alteration of warfarin effect, including elevation of prothrombin times.

7.8 CYP3A4 Inducers

Administration of CYP3A4 inducers, such as carbamazepine, rifampin and St. John's Wort, with Tramadol Hydrochloride Extended-Release may affect the metabolism of tramadol leading to reduced tramadol exposure [see CLINICAL PHARMACOLOGY (12.3) ].

Patients taking carbamazepine, a CYP3A4 inducer, may have a significantly reduced analgesic effect of tramadol. Because carbamazepine increases tramadol metabolism and because of the seizure risk associated with tramadol, concomitant administration of Tramadol Hydrochloride Extended-Release and carbamazepine is not recommended.

8 USE IN SPECIFIC POPULATIONS

8.1 Pregnancy

Teratogenic Effects: Pregnancy Category C

There are no adequate and well-controlled studies in pregnant women. Use Tramadol Hydrochloride Extended-Release during pregnancy only if the potential benefit justifies the potential risk to the fetus.

Neonatal seizures, neonatal withdrawal syndrome, fetal death and still birth have been reported during post-marketing reports with tramadol HCl immediate-release products. Tramadol Hydrochloride Extended-Release should be used during pregnancy only if the potential benefit justifies the potential risk to the fetus.

Tramadol was not teratogenic at oral dose levels up to 50 mg/kg/day (1.6-fold the maximum daily human dose (MDHD)) in rats and 100 mg/kg (approximately 6.5-fold MDHD) in rabbits during organogenesis. However, embryo-fetal lethality, reductions in fetal weight and skeletal ossification, and increased supernumerary ribs were observed at a maternal toxic dose of 140 mg/kg in mice (approximately 2.3-fold MDHD), 80 mg/kg in rats (2.6-fold MDHD) or 300 mg/kg in rabbits (approximately 19-fold MDHD).

Non-teratogenic Effects

Tramadol caused a reduction in neonatal body weight at a dose of 50 mg/kg (1.6-fold the MDHD) and reduced pup survival at an oral dose of 80 mg/kg (approximately 2.6-fold MDHD) when rats were treated during late gestation throughout lactation period.

8.2 Labor and Delivery

Tramadol Hydrochloride Extended-Release should not be used in pregnant women prior to or during labor unless the potential benefits outweigh the risks. Safe use in pregnancy has not been established. Chronic use during pregnancy may lead to physical dependence and post-partum withdrawal symptoms in the newborn [see DRUG ABUSE AND DEPENDENCE (9.1)] . Tramadol has been shown to cross the placenta. The mean ratio of serum tramadol in the umbilical veins compared to maternal veins was 0.83 for 40 women given tramadol during labor.

The effect of Tramadol Hydrochloride Extended-Release, if any, on the later growth, development, and functional maturation of the child is unknown.

8.3 Nursing Mothers

Tramadol Hydrochloride Extended-Release is not recommended for obstetrical preoperative medication or for post-delivery analgesia in nursing mothers because its safety in infants and newborns has not been studied. Following a single IV 100 mg dose of tramadol, the cumulative excretion in breast milk within 16 hours post-dose was 100 μg of tramadol (0.1% of the maternal dose) and 27 μg of M1. It is not known whether this drug is excreted in human milk following an oral dose.

8.4 Pediatric Use

The safety and efficacy of Tramadol Hydrochloride Extended-Release in patients under 18 years of age have not been established. The use of Tramadol Hydrochloride Extended-Release in the pediatric population is not recommended.

8.5 Geriatric Use

In general, caution should be used when selecting the dose for an elderly patient. Usually, dose administration should start at the low end of the dosing range, reflecting the greater frequency of decreased hepatic, renal or cardiac function and of concomitant disease or other drug therapy.

Eight hundred and twelve elderly (65 years of age or older) subjects were exposed to Tramadol Hydrochloride Extended-Release in clinical trials. Of those subjects, two hundred and forty were 75 years of age and older. In general, higher incidence rates of adverse events were observed for patients older than 65 years of age compared with patients 65 years and younger, particularly for the following adverse events: nausea, constipation, somnolence, dizziness, dry mouth, vomiting, asthenia, pruritus, anorexia sweating, fatigue, weakness, postural hypotension and dyspepsia. For this reason, Tramadol Hydrochloride Extended-Release should be used with great caution in patients older than 75 years of age [see DOSAGE AND ADMINISTRATION (2.3)].

8.6 Patients with Renal Impairment

Tramadol Hydrochloride Extended-Release has not been studied in patients with renal impairment. Impaired renal function results in a decreased rate and extent of excretion of tramadol and its active metabolite, M1. The limited availability of dose strengths of Tramadol Hydrochloride Extended-Release does not permit the dosing flexibility required for safe use in patients with severe renal impairment. Therefore, Tramadol Hydrochloride Extended-Release should not be used in patients with severe renal impairment [see DOSAGE AND ADMINISTRATION (2.3), WARNINGS AND PRECAUTIONS (5.14), and CLINICAL PHARMACOLOGY (12.3)] .

8.7 Patients with Hepatic Impairment

Tramadol Hydrochloride Extended-Release has not been studied in patients with hepatic impairment. The limited availability of dose strengths of Tramadol Hydrochloride Extended-Release does not permit the dosing flexibility required for safe use in patients with severe hepatic impairment. Therefore, Tramadol Hydrochloride Extended-Release should not be used in patients with severe hepatic impairment [see DOSAGE AND ADMINISTRATION (2.3), WARNINGS AND PRECAUTIONS, (5.14), and CLINICAL PHARMACOLOGY (12.3)].

9 DRUG ABUSE and DEPENDENCE

9.1 Controlled Substance

Tramadol Hydrochloride Extended-Release is classified as a Schedule IV controlled substance by federal regulation.

9.2 Abuse

Tramadol Hydrochloride Extended-Release contains tramadol, a mu-agonist opioid. Tramadol, like other opioids used in analgesia, can be abused and is subject to criminal diversion.

Addiction is a primary, chronic, neurobiologic disease, with genetic, psychosocial, and environmental factors influencing its development and manifestations. It is characterized by behaviors that include one or more of the following: impaired control over drug use, compulsive use, continued use despite harm, and craving. Drug addiction is a treatable disease, utilizing a multidisciplinary approach, but relapse is common.

“Drug-seeking” behavior is very common in addicts and drug abusers. Drug-seeking tactics include emergency calls or visits near the end of office hours, refusal to undergo appropriate examination, testing or referral, repeated “loss” of prescriptions, tampering with prescriptions and reluctance to provide prior medical records or contact information for other treating physician(s). “Doctor shopping” to obtain additional prescriptions is common among drug abusers and people suffering from untreated addiction.

Abuse and addiction are separate and distinct from physical dependence and tolerance. Physicians should be aware that addiction may not be accompanied by concurrent tolerance and symptoms of physical dependence in all addicts. In addition, abuse of opioids can occur in the absence of true addiction and is characterized by misuse for non-medical purposes, often in combination with other psychoactive substances. Tramadol Hydrochloride Extended-Release, like other opioids, may be diverted for non-medical use. Careful record keeping of prescribing information, including quantity, frequency, and renewal requests is strongly advised.

Proper assessment of the patient, proper prescribing practices, periodic re-evaluation of therapy, and proper dispensing and storage are appropriate measures that help to limit abuse of opioid drugs.

Tramadol Hydrochloride Extended-Release is intended for oral use only. The crushed capsule poses a hazard of overdose and death. This risk is increased with concurrent abuse of alcohol and other substances. With parenteral abuse, the capsule excipients can be expected to result in local tissue necrosis, infection, pulmonary granulomas, and increased risk of endocarditis and valvular heart injury. Parenteral drug abuse is commonly associated with transmission of infectious diseases such as hepatitis and HIV.

Use in Drug and Alcohol Addiction

Tramadol Hydrochloride Extended-Release is an opioid with no approved use for the management of addictive disorders. Its proper usage in individuals with drug or alcohol dependence, either active or in remission is for the management of pain requiring opioid analgesia. Concerns about abuse and addiction should not prevent the proper management of pain. However all patients treated with opioids require careful monitoring for signs of abuse and addiction, because use of opioid analgesic products carries the risk of addiction even under appropriate medical use.

9.3 Dependence

Tolerance is the need for increasing doses of opioids to maintain a defined effect such as analgesia (in the absence of disease progression or other external factors). Physical dependence is manifested by withdrawal symptoms after abrupt discontinuation of a drug or upon administration of an antagonist.

Withdrawal Symptoms

The opioid abstinence or withdrawal syndrome is characterized by some or all of the following: restlessness, lacrimation, rhinorrhea, yawning, perspiration, chills, myalgia, and mydriasis. Other symptoms also may develop, including irritability, anxiety, backache, joint pain, weakness, abdominal cramps, insomnia, nausea, anorexia, vomiting, diarrhea, or increased blood pressure, respiratory rate, or heart rate.

Generally, tolerance and/or withdrawal are more likely to occur the longer a patient is on continuous opioid therapy.

Withdrawal symptoms may occur if Tramadol Hydrochloride Extended-Release is discontinued abruptly. Onset of adverse events are likely to occur after treatment is stopped. These symptoms may include: anxiety, sweating, insomnia, rigors, pain, nausea, tremors, diarrhea, upper respiratory symptoms, piloerection, and rarely hallucinations. Clinical experiences with tramadol suggests that withdrawal symptoms may be reduced by tapering Tramadol Hydrochloride Extended-Release when discontinuing tramadol therapy [ see DOSAGE AND ADMINISTRATION (2) and WARNINGS AND PRECAUTIONS (5.10) ].

10 OVERDOSAGE

10.1 Human Experience

Acute overdosage with tramadol can be manifested by respiratory depression, somnolence progressing to stupor or coma, skeletal muscle flaccidity, cold and clammy skin, constricted pupils, bradycardia, hypotension, and death.

Deaths due to overdose have been reported with abuse and misuse of tramadol, by ingesting, inhaling, or injecting the crushed tablets. Review of case reports has indicated that the risk of fatal overdose is further increased when tramadol is abused concurrently with alcohol or other CNS depressants, including other opioids.

10.2 Management of Overdose

In the treatment of tramadol overdosage, primary attention should be given to the reestablishment of a patent airway and institution of assisted or controlled ventilation. Supportive measures (including oxygen and vasopressors) should be employed in the management of circulatory shock and pulmonary edema accompanying overdose as indicated. Cardiac arrest or arrhythmias may require cardiac massage or defibrillation.

While naloxone will reverse some, but not all, symptoms caused by overdosage with tramadol, the risk of seizures is also increased with naloxone administration. In animals, convulsions following the administration of toxic doses of Tramadol Hydrochloride Extended-Release could be suppressed with barbiturates or benzodiazepines but were increased with naloxone. Naloxone administration did not change the lethality of an overdose in mice. Hemodialysis is not expected to be helpful in an overdose because it removes less than 7% of the administered dose in a 4-hour dialysis period.

11 DESCRIPTION

Tramadol Hydrochloride Extended-Release (tramadol hydrochloride) capsules is a centrally acting synthetic analgesic in an extended-release oral formulation. The chemical name for tramadol hydrochloride is (±) cis-2-[(dimethylamino)methyl]-1-(3-methoxyphenyl) cyclohexanol hydrochloride. Its structural formula is:

Figure 1

The molecular weight of tramadol hydrochloride is 299.8. It is a white, bitter, crystalline and odorless powder that is readily soluble in water and ethanol and has a pKa of 9.41. The n-octanol/water log partition coefficient (logP) is 1.35 at pH 7. Tramadol Hydrochloride Extended-Release capsules contain a total dose of tramadol HCl 100, 200 and 300 mg in a combination of immediate-release and extended-release components.

Dosage | Immediate-release | Extended-release
150 mg | 37.5 mg | 112.5 mg

Tramadol Hydrochloride Extended-Release capsules are white in color. Inactive ingredients include gelatin, titanium dioxide, shellac, yellow iron oxide, lactose monohydrate 200 mesh, microcrystalline cellulose, povidone K30, corn starch, sodium starch glycolate, magnesium stearate, sucrose stearate, hypromellose, talc, polysorbate 80, Eudragit NE 30D, and simethicone emulsion.

12 CLINICAL PHARMACOLOGY

12.1 Mechanism of Action

Tramadol Hydrochloride Extended-Release contains tramadol, a centrally acting synthetic opioid analgesic. Although its mode of action is not completely understood, from animal tests, at least two complementary mechanisms appear applicable: binding of parent and M1 metabolite to μ-opioid receptors and weak inhibition of reuptake of norepinephrine and serotonin.

Opioid activity is due to both low affinity binding of the parent compound and higher affinity binding of the O-demethylated metabolite M1 to μ-opioid receptors. In animal models, M1 is up to 6 times more potent than tramadol in producing analgesia and 200 times more potent in μ-opioid binding. Tramadol-induced analgesia is only partially antagonized by the opiate antagonist naloxone in several animal tests. The relative contribution of both tramadol and M1 to human analgesia is dependent upon the plasma concentrations of each compound.

12.2 Pharmacodynamics

Tramadol has been shown to inhibit reuptake of norepinephrine and serotonin in vitro, as have some other opioid analgesics. These mechanisms may contribute independently to the overall analgesic profile of tramadol. The relationship between exposure of tramadol and M1 and efficacy has not been evaluated in clinical studies.

Apart from analgesia, tramadol administration may produce a constellation of symptoms (including dizziness, somnolence, nausea, constipation, sweating and pruritus) similar to that of other opioids. In contrast to morphine, tramadol has not been shown to cause histamine release. At therapeutic doses, tramadol has no effect on heart rate, left ventricular function or cardiac index. Orthostatic hypotension has been observed.

12.3 Pharmacokinetics

The analgesic activity of tramadol is due to both parent drug and the M1 metabolite. Tramadol Hydrochloride Extended-Release is administered as a racemate and both tramadol and M1 are detected in the circulation. The Cmax and AUC of Tramadol Hydrochloride Extended-Release capsules have been observed to be dose-proportional over an oral dose range of 100 to 300 mg in healthy subjects.

Absorption:

After a single dose administration of Tramadol Hydrochloride Extended-Release, Tmax occurs around 10-12 hours.

The mean Cmax and AUC of Tramadol Hydrochloride Extended-Release capsules after a 300 mg single dose was 308 ng/mL and 6777 ng*hr/mL, respectively under fasting conditions. Tramadol Hydrochloride Extended-Release is bioequivalent to a reference extended-release tramadol product following a single 300 mg dose under fasting conditions.

At steady-state, Tramadol Hydrochloride Extended-Release at 200 mg has been observed to be bioequivalent to a reference extended-release tramadol product at 200 mg under fasting conditions (Table 2). Following administration of Tramadol Hydrochloride Extended-Release 200 mg capsules, steady-state plasma concentrations of both tramadol and M1 are achieved within four days of once daily dosing.

Table 2.
Mean (%CV) Steady-State Pharmacokinetic Parameter Values (N= 38)
 | Tramadol |  | O-Desmethyl-Tramadol (M1 Metabolite)
Parameter | Tramadol hydrochloride Extended Release Capsules 200 mg | A Reference Extended-Release Tramadol Product 200 mg | Tramadol hydrochloride Extended Release Capsules 200 mg | A Reference Extended-Release Tramadol Product 200 mg
AUC0-24 (ng.h/mL) | 5678 (27%) | 5563 (32%) | 1319 (34%) | 1302 (40%)
Cmax (ng/mL) | 332 (25%) | 350 (31%) | 70 (34%) | 74 (41%)
Cmin (ng/mL) | 128 (39%) | 125 (45%) | 35 (34%) | 33 (42%)
Tmax | 5.9 (66%) | 10 (30%) | 11 (37%) | 13 (29%)
% Fluctuation | 88 (19%) | 101 (30%) | 64 (22%) | 76 (30%)
AUC0-24: Area Under the Curve in a 24-hour dosing interval
Cmax: Peak Concentration in a 24-hour dosing interval
Cmin: Trough Concentration in a 24-hour dosing interval
Tmax: Time to Peak Concentration

Food Effects:

The rate and extent of absorption of Tramadol Hydrochloride Extended-Release capsules (300 mg) are similar following oral administration with or without food. Therefore, Tramadol Hydrochloride Extended-Release capsules can be administered without regard to meals.

Distribution:

The volume of distribution of tramadol was 2.6 and 2.9 liters/kg in male and female subjects, respectively, following a 100 mg intravenous tramadol dose. The binding of tramadol to human plasma proteins is approximately 20% and binding also appears to be independent of concentration up to 10 μg/mL. Saturation of plasma protein binding occurs only at concentrations outside the clinically relevant range.

Metabolism:

Tramadol is extensively metabolized after oral administration. The major metabolic pathways appear to be N – (mediated by CYP3A4 and CYP2B6) and O – (mediated by CYP2D6) demethylation and glucuronidation or sulfation in the liver. One metabolite (O-desmethyl tramadol, denoted M1) is pharmacologically active in animal models. Formation of M1 is dependent on CYP2D6 and as such is subject to inhibition and polymorphism, which may affect the therapeutic response [see DRUG INTERACTIONS (7)] .

Elimination:

Tramadol is eliminated primarily through metabolism by the liver and the metabolites are eliminated primarily by the kidneys. Approximately 30% of the dose is excreted in the urine as unchanged drug, whereas 60% of the dose is excreted as metabolites. The remainder is excreted either as unidentified or as unextractable metabolites. The mean plasma elimination half-lives of racemic tramadol and racemic M1 after administration of Tramadol Hydrochloride Extended-Release capsules are approximately 10 and 11 hours, respectively.

Special Populations:

Renal Impairment

Impaired renal function results in a decreased rate and extent of excretion of tramadol and its active metabolite, M1. The pharmacokinetics of tramadol was studied in patients with mild or moderate renal impairment after receiving multiple doses of an extended-release tramadol product at 100 mg. There is no consistent trend observed for tramadol exposure related to renal function in patients with mild (CLcr: 50-80 mL/min) or moderate (CLcr: 30-50 mL/min) renal impairment in comparison to patients with normal renal function (CLcr > 80 mL/min). However, exposure of M1 increased 20-40% with increased severity of the renal impairment (from normal to mild and moderate). The pharmacokinetics of tramadol has not been studied in patients with severe renal impairment (CLcr < 30 mL/min). The limited availability of dose strengths of Tramadol Hydrochloride Extended-Release does not permit the dosing flexibility required for safe use in patients with severe renal impairment. Therefore, Tramadol Hydrochloride Extended-Release should not be used in patients with severe renal impairment [see DOSAGE AND ADMINISTRATION (2.3), WARNINGS AND PRECAUTIONS (5.14) and USE IN SPECIFIC POPULATIONS (8.6)]. The total amount of tramadol and M1 removed during a 4-hour dialysis period is less than 7% of the administered dose.

Hepatic Impairment

Pharmacokinetics of tramadol was studied in patients with mild or moderate hepatic impairment after receiving multiple doses of an extended-release tramadol product at 100 mg. The exposure of (+)- and (-)-tramadol was similar in mild and moderate hepatic impairment patients in comparison to patients with normal hepatic function. However, exposure of (+)- and (-)-M1 decreased ~50% with increased severity of the hepatic impairment (from normal to mild and moderate). The pharmacokinetics of tramadol has not been studied in patients with severe hepatic impairment. After the administration of tramadol immediate-release tablets to patients with advanced cirrhosis of the liver, tramadol area under the plasma concentration time curve was larger and the tramadol and M1 half-lives were longer than subjects with normal hepatic function. The limited availability of dose strengths of Tramadol Hydrochloride Extended-Release does not permit the dosing flexibility required for safe use in patients with severe hepatic impairment. Therefore, Tramadol Hydrochloride Extended-Release should not be used in patients with severe hepatic impairment [see DOSAGE AND ADMINISTRATION (2.3), WARNINGS AND PRECAUTIONS (5.14), and USE IN SPECIFIC POPULATIONS (8.7)].

Gender

Based on pooled multiple-dose pharmacokinetics studies for an extended-release tramadol product in 166 healthy subjects (111 males and 55 females), the dose-normalized AUC values for tramadol were somewhat higher in females than in males. There was a considerable degree of overlap in values between male and female groups. Dosage adjustment based on gender is not recommended.

Age

The effect of age on pharmacokinetics of Tramadol Hydrochloride Extended-Release has not been studied. Healthy elderly subjects aged 65 to 75 years administered an immediate-release formulation of tramadol, have plasma concentrations and elimination half-lives comparable to those observed in healthy subjects less than 65 years of age. In subjects over 75 years, mean maximum plasma concentrations are elevated (208 vs. 162 ng/mL) and the mean elimination half-life is prolonged (7 vs. 6 hours) compared to subjects 65 to 75 years of age. Adjustment of the daily dose is recommended for patients older than 75 years [see DOSAGE AND ADMINISTRATION (2.3)].

Drug Interactions:

Poor / Extensive Metabolizers, CYP2D6

The formation of the active metabolite, M1, is mediated by CYP2D6, a polymorphic enzyme. Approximately 7% of the population has reduced activity of the CYP2D6 isoenzyme of cytochrome P-450 metabolizing enzyme system. These individuals are “poor metabolizers” of debrisoquine, dextromethorphan and tricyclic antidepressants, among other drugs. Based on a population PK analysis of Phase 1 studies with IR tablets in healthy subjects, concentrations of tramadol were approximately 20% higher in "poor metabolizers" versus "extensive metabolizers," while M1 concentrations were 40% lower.

CYP2D6 Inhibitors

In vitro drug interaction studies in human liver microsomes indicate that concomitant administration with inhibitors of CYP2D6 such as fluoxetine, paroxetine, and amitriptyline could result in some inhibition of the metabolism of tramadol.

Quinidine

Tramadol is metabolized to active metabolite M1 by CYP2D6. Coadministration of quinidine, a selective inhibitor of CYP2D6, with tramadol ER resulted in a 50-60% increase in tramadol exposure and a 50-60% decrease in M1 exposure. The clinical consequences of these findings are unknown.

To evaluate the effect of tramadol, a CYP2D6 substrate on quinidine, an in vitro drug interaction study in human liver microsomes was conducted. The results from this study indicate that tramadol has no effect on quinidine metabolism.

[see WARNINGS AND PRECAUTIONS (5.1, 5.3) and DRUG INTERACTIONS (7.3) ].

CYP3A4 Inhibitors and Inducers

Since tramadol is also metabolized by CYP3A4, administration of CYP3A4 inhibitors, such as ketoconazole and erythromycin, or CYP3A4 inducers, such as rifampin and St. John's Wort, with Tramadol Hydrochloride Extended-Release may affect the metabolism of tramadol leading to altered tramadol exposure [see WARNINGS AND PRECAUTIONS (5.1, 5.3) and DRUG INTERACTIONS (7.3) ].

Cimetidine

Concomitant administration of tramadol immediate-release tablets with cimetidine, a weak CPY3A4 inhibitor, does not result in clinically significant changes in tramadol pharmacokinetics. No alteration of the Tramadol Hydrochloride Extended-Release dosage regimen with cimetidine is recommended.

Carbamazepine

Carbamazepine, a CYP3A4 inducer, increases tramadol metabolism. Patients taking carbamazepine may have a significantly reduced analgesic effect of tramadol. Concomitant administration of Tramadol Hydrochloride Extended-Release and carbamazepine is not recommended.

13 NON-CLINICAL TOXICOLOGY

13.1 Carcinogenesis, Mutagenesis, Impairment of Fertility

Carcinogenicity assessment has been conducted in mice, rats and p53(+/-) heterozygous mice. A slight, but statistically significant, increase in two common murine tumors, pulmonary and hepatic, was observed in a mouse carcinogenicity study, particularly in aged mice. Mice were dosed orally up to 30 mg/kg (90 mg/m^2 or 0.5 times the maximum daily human dosage of 185 mg/m^2) for approximately two years, although the study was not done with the Maximum Tolerated Dose. This finding is not believed to suggest risk in humans.

No treatment-related tumors were noted in a rat carcinogenicity study (dosing orally up to 30 mg/kg, 180 mg/m^2, or equivalent to the maximum daily human dosage) or in a second study where rats were treated with up to 75 mg/kg/day for males and 100 mg/kg/day for females (approximately 2.4 and 3.2-fold MDHD, respectively) for two years. However, the excessive decrease in body weight gain observed in the rat study might have reduced their sensitivity to any potential carcinogenic effect of the drug.

No carcinogenic effect of tramadol was observed in p53(+/–)-heterozygous mice at oral doses up to 150 mg/kg/day (approximately 2.4-fold maximum daily human dose [MDHD] of 300 mg/day for a 60 kg adult based on body surface conversion) for 26 weeks.

Tramadol was not mutagenic in the following assays: a bacterial reverse mutation assay using Salmonella and E. coli, a mouse lymphoma assay (in the absence of metabolic activation), chromosomal aberration test in Chinese hamsters, a bone marrow micronucleus test in mice and Chinese hamsters, and a dominant lethal mutation test in mice. Mutagenic results occurred in the presence of metabolic activation in the mouse lymphoma assay and micronucleus test in rats. Overall, the weight of evidence from these tests indicates that tramadol does not pose a genotoxic risk to humans.

No effects on fertility were observed for tramadol at oral dose levels up to 50 mg/kg/day in male and female rats (1.6-fold the MDHD).

14 CLINICAL STUDIES

Tramadol Hydrochloride Extended-Release is bioequivalent under fasting conditions to another extended-release tramadol product [see CLINICAL PHARMACOLOGY (12.3)] which did demonstrate efficacy in two of four clinical trials of patients with chronic pain. To qualify for inclusion into these studies, patients were required to have moderate to moderately severe pain as defined by a pain intensity score of ≥40 mm, off previous medications, on a 0 – 100 mm visual analog scale (VAS).

In one 12-week randomized, double-blind, placebo-controlled study, patients with moderate to moderately severe pain due to osteoarthritis of the knee and/or hip were administered doses from 100 mg to 400 mg daily. Treatment with the extended-release tramadol product was initiated at 100 mg once daily for four days then increased by 100 mg per day increments every five days to the randomized fixed dose. Between 51% and 59% of patients in active treatment groups completed the study and 56% of patients in the placebo group completed the study. Discontinuations due to adverse events were more common in the extended-release tramadol product 200 mg, 300 mg and 400 mg treatment groups (20%, 27%, and 30% of discontinuations, respectively) compared to 14% of the patients treated with the extended-release tramadol product 100 mg and 10% of patients treated with placebo.

Pain, as assessed by the WOMAC Pain subscale, was measured at 1, 2, 3, 6, 9, and 12 weeks and change from baseline assessed. A responder analysis based on the percent change in WOMAC Pain subscale demonstrated a statistically significant improvement in pain for the 100 mg and 200 mg treatment groups compared to placebo (see Figure 2).

Figure 2

In one 12-week randomized, double-blind, placebo-controlled flexible-dosing trial of the extended-release tramadol product in patients with osteoarthritis of the knee, patients titrated to an average daily dose of approximately 270 mg/day. Forty-nine percent of patients randomized to the active treatment group completed the study, while 52% of patients randomized to placebo completed the study. Most of the early discontinuations in the active treatment group were due to adverse events, accounting for 27% of the early discontinuations in contrast to 7% of the discontinuations from the placebo group. Thirty-seven percent of the placebo-treated patients discontinued the study due to lack of efficacy compared to 15% of active-treated patients. The active treatment group demonstrated a statistically significant decrease in the mean Visual Analog Scale (VAS) score, and a statistically significant difference in the responder rate, based on the percent change from baseline in the VAS score, measured at 1, 2, 4, 8, and 12 weeks, between patients receiving the extended-release tramadol product and placebo (see Figure 3).

Figure 3

Four randomized, placebo-controlled clinical trials of Tramadol Hydrochloride Extended-Release were conducted, none of which demonstrated efficacy but which differed in design from the preceding clinical studies described. Two trials were 12-week randomized placebo-controlled trials of Tramadol Hydrochloride Extended-Release 100 mg/day, 200 mg/day, and 300 mg/day versus placebo in patients with moderate to moderately severe osteoarthritis pain of the hip and knee. The other two 12 week trials were similar in design, but only studied Tramadol Hydrochloride Extended-Release 300 mg/day. In this fixed-dose design, subjects were required to titrate to a fixed dose, even if their pain responded to a lower titration dose.

16 HOW SUPPLIED/STORAGE AND HANDLING

Tramadol Hydrochloride Extended-Release capsules are supplied as opaque white hard gelatin capsules, imprinted as follows.

150 mg Capsules: White capsule imprinted with gold ink “ G 322” on cap and “ 150” between lines on the body

Repackaged by:

Medsource Pharmaceuticals

Rancho Santa Margarita, CA 92688

Storage

Dispense in a tight container. Store at 25°C; excursions permitted to 15°C to 30°C (59°F to 86°F). Keep out of reach of children.

17 PATIENT COUNSELING INFORMATION

Inform patients that:

- Tramadol Hydrochloride Extended-Release is for oral use only and should be swallowed whole. The capsule should not be chewed, dissolved, crushed or split.
- Tramadol Hydrochloride Extended-Release may cause seizures and/or serotonin syndrome with concomitant use of serotonergic agents (including SRIs, NRIs, and triptans) or drugs that significantly reduce the metabolic clearance of tramadol.
- Not to change the prescribed single-dose or 24-hour dosing regimen of Tramadol Hydrochloride Extended-Release, and that exceeding the prescribed dose can result in respiratory depression, seizures or death.
- Tramadol Hydrochloride Extended-Release may impair mental or physical abilities required for the performance of potentially hazardous tasks such as driving a car or operating machinery.
- Tramadol Hydrochloride Extended-Release should not be taken with alcohol containing beverages.
- Tramadol Hydrochloride Extended-Release should be used with caution when taking medications such as tranquilizers, hypnotics or other opiate containing analgesics.
- Instruct female patients to inform the prescriber if they are pregnant, think they might become pregnant, or are trying to become pregnant.
- Tramadol Hydrochloride Extended-Release is to be taken once-a-day and at approximately the same time every day. Also, exceeding these recommendations and the maximum recommended daily dose can result in respiratory depression, seizures or death.
- Elderly patients, especially those over 75 years of age, and other patients who have renal or hepatic impairments may need to be cautioned about reduced dosages.
- Not to abruptly withdraw or discontinue tramadol therapy, as clinical experience with tramadol suggests the possible onset of signs and symptoms of withdrawal. These affects may be reduced by tapering tramadol therapy.
- Tramadol Hydrochloride Extended-Release must be kept out of reach of children.

Revised: 06/2011

Principal Display Panel - 60 count

TRAMADOL HCL ER CAPSULES 150MG #60

CIV

NDC: 45865-0709-60